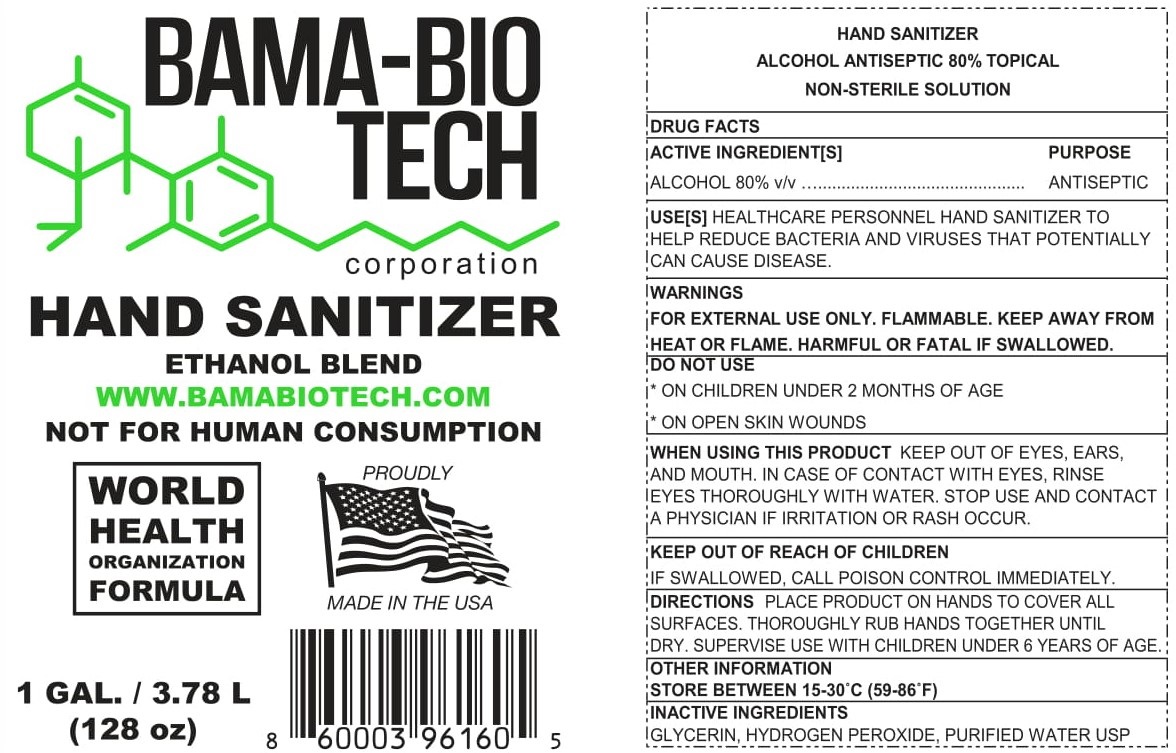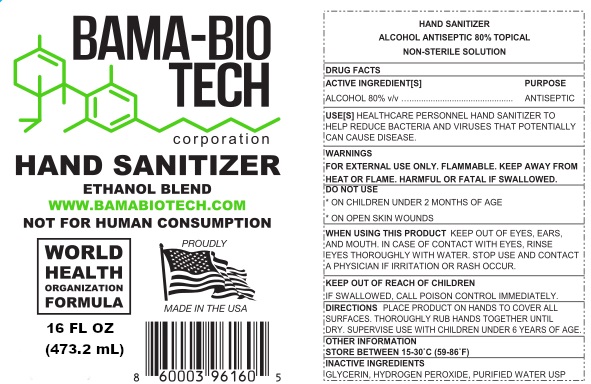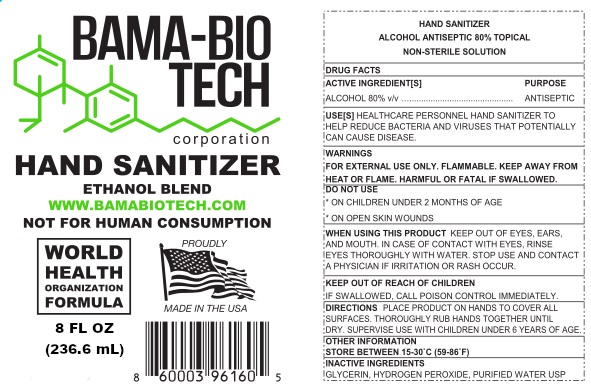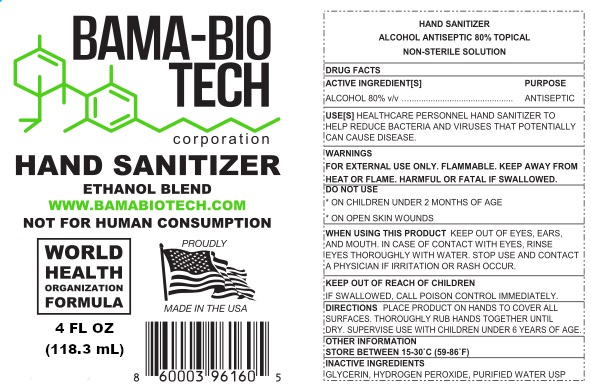 DRUG LABEL: Bama-Bio Tech Hand Sanitizer 80 Ethanol Unscented
NDC: 90085-000 | Form: LIQUID
Manufacturer: Bama-Bio Tech Corporation
Category: otc | Type: HUMAN OTC DRUG LABEL
Date: 20220105

ACTIVE INGREDIENTS: ALCOHOL 0.8 mL/1 mL
INACTIVE INGREDIENTS: GLYCERIN; HYDROGEN PEROXIDE; WATER

Bama-Bio Tech Hand Sanitizer 80% Ethanol Unscented

ACTIVE INGREDIENT[S]

ALCOHOL 80% v/v

PURPOSE

ANTISEPTIC

USE[S]

HEALTHCARE PERSONNEL HAND SANITIZER TO HELP REDUCE BACTERIA AND VIRUSES THAT POTENTIALLY CAN CAUSE DISEASE.

WARNINGS

FOR EXTERNAL USE ONLY. FLAMMABLE. KEEP AWAY FROM HEAT OR FLAME. HARMFUL OR FATAL IF SWALLOWED.

DO NOT USE

- ON CHILDREN UNDER 2 MONTHS OF AGE
- ON OPEN SKIN WOUNDS

WHEN USING THIS PRODUCT

KEEP OUT OF EYES, EARS, AND MOUTH. IN CASE OF CONTACT WITH EYES, RINSE EYES THOROUGHLY WITH WATER.

STOP USE AND CONTACT A PHYSICIAN

IF IRRITATION OR RASH OCCUR.

KEEP OUT OF REACH OF CHILDREN

IF SWALLOWED, CALL POISON CONTROL IMMEDIATELY.

DIRECTIONS

PLACE PRODUCT ON HANDS TO COVER ALL SURFACES. THOROUGHLY RUB HANDS TOGETHER UNTIL DRY. SUPERVISE USE WITH CHILDREN UNDER 6 YEARS OF AGE.

OTHER INFORMATION

STORE BETWEEN 15-30°C (59-86°F)

INACTIVE INGREDIENTS

GLYCERIN, HYDROGEN PEROXIDE, PURIFIED WATER USP